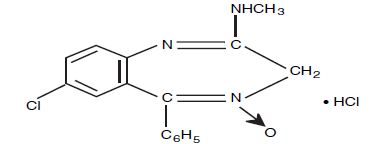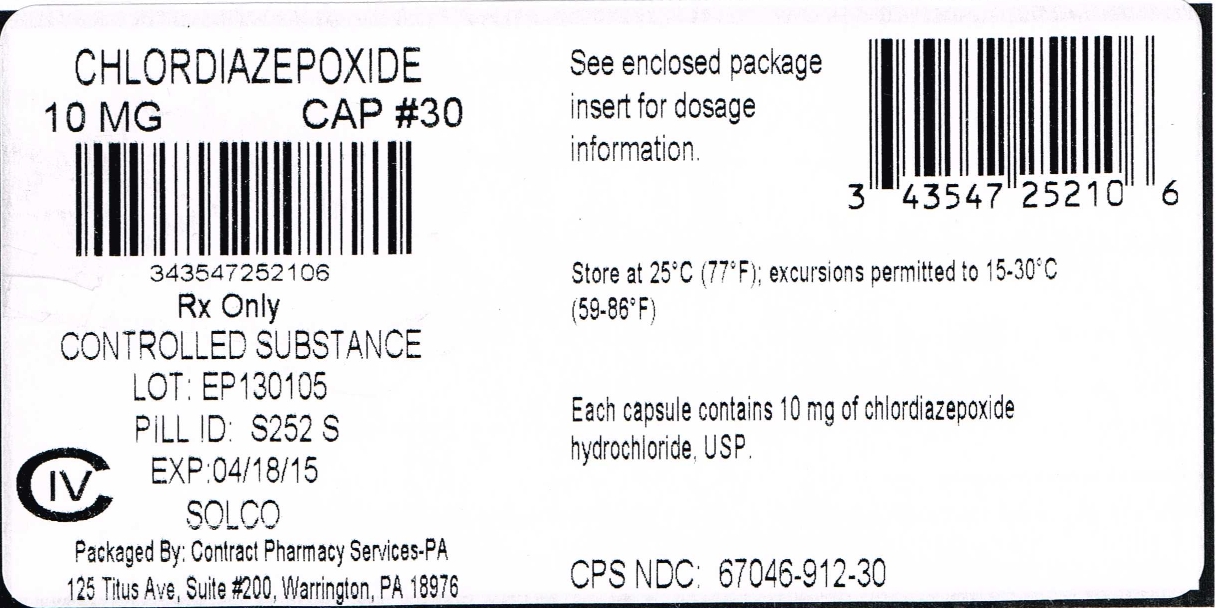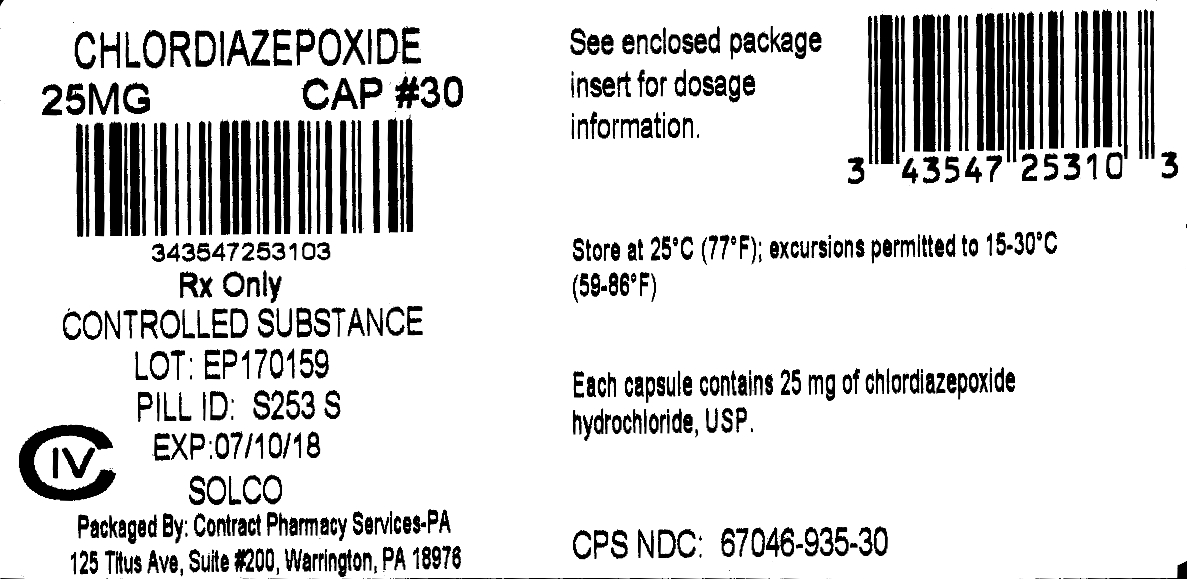 DRUG LABEL: Chlordiazepoxide Hydrochloride
NDC: 67046-912 | Form: CAPSULE, GELATIN COATED
Manufacturer: Contract Pharmacy Services-PA
Category: prescription | Type: HUMAN PRESCRIPTION DRUG LABEL
Date: 20170831
DEA Schedule: CIV

ACTIVE INGREDIENTS: CHLORDIAZEPOXIDE HYDROCHLORIDE 10 mg/1 1
INACTIVE INGREDIENTS: STARCH, CORN; LACTOSE MONOHYDRATE; TALC; METHYLPARABEN; PROPYLPARABEN; POTASSIUM SORBATE; D&C YELLOW NO. 10; FD&C BLUE NO. 1; FD&C GREEN NO. 3; FD&C YELLOW NO. 6; FD&C RED NO. 40; TITANIUM DIOXIDE; GELATIN

Chlordiazepoxide Hydrochloride Capsules, USP 912 935
Gelatin Coated

Rx only

DESCRIPTION:

Chlordiazepoxide Hydrochloride Capsules, USP, the original Chlordiazepoxide Hydrochloride and prototype for the benzodiazepine compounds, was synthesized and developed at Hoffmann-La Roche Inc. It is a versatile therapeutic agent of proven value for the relief of anxiety. Chlordiazepoxide Hydrochloride Capsule is among the safer of the effective psychopharmacologic compounds available, as demonstrated by extensive clinical evidence.

Chlordiazepoxide Hydrochloride is available as capsules containing 5 mg, 10 mg or 25 mg chlordiazepoxide hydrochloride. Each capsule also contains corn starch, lactose monohydrate and talc. Gelatin capsule shells may contain methyl and propyl parabens, Titanium Dioxide, Gelatin and potassium sorbate, with the following dye systems: 5-mg capsules - FD&C Yellow No. 6 plus D&C Yellow No. 10 and FD&C Green No. 3. 10-mg capsules - D&C Yellow No. 10, FD&C Blue No. 1, FD&C Green No. 3, FD&C Yellow No. 6 plus FD&C Red No. 40. 25-mg capsules - D&C Yellow No. 10 and FD&C Green No. 3.

Chlordiazepoxide hydrochloride is 7-chloro-2-(methylamino)-5-phenyl-3H-1,4-benzodiazepine 4-oxide hydrochloride. A white to practically white crystalline substance, it is soluble in water. It is unstable in solution and the powder must be protected from light. The molecular weight is 336.22. The structural formula of chlordiazepoxide hydrochloride is as follows:

CLINICAL PHARMACOLOGY:

Chlordiazepoxide hydrochloride has antianxiety, sedative, appetite-stimulating and weak analgesic actions. The precise mechanism of action is not known. The drug blocks EEG arousal from stimulation of the brain stem reticular formation. It takes several hours for peak blood levels to be reached and the half-life of the drug is between 24 and 48 hours. After the drug is discontinued plasma levels decline slowly over a period of several days. Chlordiazepoxide is excreted in the urine, with 1% to 2% unchanged and 3% to 6% as conjugate.

Animal Pharmacology:

The drug has been studied extensively in many species of animals and these studies are suggestive of action on the limbic system of the brain, which recent evidence indicates is involved in emotional responses.

Hostile monkeys were made tame by oral drug doses which did not cause sedation. Chlordiazepoxide hydrochloride revealed a “taming” action with the elimination of fear and aggression. The taming effect of chlordiazepoxide hydrochloride was further demonstrated in rats made vicious by lesions in the septal area of the brain. The drug dosage which effectively blocked the vicious reaction was well below the dose which caused sedation in these animals.

The LD50 of parenterally administered chlordiazepoxide hydrochloride was determined in mice (72 hours) and rats (5 days), and calculated according to the method of Miller and Tainter, with the following results: mice, IV, 123 ±12mg/kg; mice, IM, 366±7mg/kg; rats, IV, 120±7 mg/kg; rats, IM, >160 mg/kg.

Effects on Reproduction:

Reproduction studies in rats fed 10, 20 and 80 mg/kg daily and bred through one or two matings showed no congenital anomalies, nor were there adverse effects on lactation of the dams or growth of the newborn. However, in another study at 100 mg/kg daily there was noted a significant decrease in the fertilization rate and a marked decrease in the viability and body weight of offspring which may be attributable to sedative activity, thus resulting in lack of interest in mating and lessened maternal nursing and care of the young. One neonate in each of the first and second matings in the rat reproduction study at the 100 mg/kg dose exhibited major skeletal defects. Further studies are in progress to determine the significance of these findings.

INDICATIONS AND USAGE:

Chlordiazepoxide Hydrochloride Capsule is indicated for the management of anxiety disorders or for the short term relief of symptoms of anxiety, withdrawal symptoms of acute alcoholism, and preoperative apprehension and anxiety. Anxiety or tension associated with the stress of everyday life usually does not require treatment with an anxiolytic.

The effectiveness of Chlordiazepoxide Hydrochloride Capsule in long-term use, that is, more than 4 months, has not been assessed by systematic clinical studies. The physician should periodically reassess the usefulness of the drug for the individual patient.

CONTRAINDICATIONS:

Chlordiazepoxide Hydrochloride Capsule is contraindicated in patients with known hypersensitivity to the drug.

WARNINGS:

Chlordiazepoxide hydrochloride may impair the mental and/or physical abilities required for the performance of potentially hazardous tasks such as driving a vehicle or operating machinery. Similarly, it may impair mental alertness in children. The concomitant use of alcohol or other central nervous system depressants may have an additive effect. PATIENTS SHOULD BE WARNED ACCORDINGLY.

Usage in Pregnancy: An increased risk of congenital malformations associated with the use of minor tranquilizers (chlordiazepoxide, diazepam and meprobamate) during the first trimester of pregnancy has been suggested in several studies. Because use of these drugs is rarely a matter of urgency, their use during this period should almost always be avoided. The possibility that a woman of childbearing potential may be pregnant at the time of institution of therapy should be considered. Patients should be advised that if they become pregnant during therapy or intend to become pregnant they should communicate with their physicians about the desirability of discontinuing the drug.

Withdrawal symptoms of the barbiturate type have occurred after the discontinuation of benzodiazepines. (See DRUG ABUSE AND DEPENDENCE section.)

PRECAUTIONS:

In elderly and debilitated patients, it is recommended that the dosage be limited to the smallest effective amount to preclude the development of ataxia or oversedation (10 mg or less per day initially, to be increased gradually as needed and tolerated). In general, the concomitant administration of Chlordiazepoxide hydrochloride and other psychotropic agents is not recommended. If such combination therapy seems indicated, careful consideration should be given to the pharmacology of the agents to be employed - particularly when the known potentiating compounds such as MAO inhibitors and phenothiazines are to be used. The usual precautions in treating patients with impaired renal or hepatic function should be observed.

Paradoxical reactions, e.g., excitement, stimulation and acute rage, have been reported in psychiatric patients and in hyperactive aggressive pediatric patients, and should be watched for during Chlordiazepoxide hydrochloride therapy. The usual precautions are indicated when Chlordiazepoxide hydrochloride is used in the treatment of anxiety states where there is any evidence of impending depression; it should be borne in mind that suicidal tendencies may be present and protective measures may be necessary. Although clinical studies have not established a cause and effect relationship, physicians should be aware that variable effects on blood coagulation have been reported very rarely in patients receiving oral anticoagulants and Chlordiazepoxide hydrochloride. In view of isolated reports associating chlordiazepoxide with exacerbation of porphyria, caution should be exercised in prescribing chlordiazepoxide to patients suffering from this disease.

Pediatric Use:

Because of the varied response of pediatric patients to CNS-acting drugs, therapy should be initiated with the lowest dose and increased as required (see DOSAGE AND ADMINISTRATION).

Since clinical experience with Chlordiazepoxide hydrochloride in pediatric patients under 6 years of age is limited, use in this age group is not recommended. Hyperactive aggressive pediatric patients should be monitored for paradoxical reactions to Chlordiazepoxide hydrochloride (see PRECAUTIONS).

Information for Patients:

To assure the safe and effective use of benzodiazepines, patients should be informed that, since benzodiazepines may produce psychological and physical dependence, it is advisable that they consult with their physician before either increasing the dose or abruptly discontinuing this drug.

ADVERSE REACTIONS:

The necessity of discontinuing therapy because of undesirable effects has been rare. Drowsiness, ataxia and confusion have been reported in some patients - particularly the elderly and debilitated. While these effects can be avoided in almost all instances by proper dosage adjustment, they have occasionally been observed at the lower dosage ranges. In a few instances syncope has been reported.

Other adverse reactions reported during therapy include isolated instances of skin eruptions, edema, minor menstrual irregularities, nausea and constipation, extra pyramidal symptoms, as well as increased and decreased libido. Such side effects have been infrequent, and are generally controlled with reduction of dosage. Changes in EEG patterns (low-voltage fast activity) have been observed in patients during and after Chlordiazepoxide hydrochloride treatment.

Blood dyscrasias (including agranulocytosis), jaundice and hepatic dysfunction have occasionally been reported during therapy. When Chlordiazepoxide hydrochloride treatment is protracted, periodic blood counts and liver function tests are advisable.

To report SUSPECTED ADVERSE REACTIONS, contact 1-800-321-4576 or FDA at 1-800-FDA-1088 or www.fda.gov/medwatch.

DRUG ABUSE AND DEPENDENCE:

Chlordiazepoxide hydrochloride capsules are classified by the Drug Enforcement Administration as a Schedule IV controlled substance.

Withdrawal symptoms, similar in character to those noted with barbiturates and alcohol (convulsions, tremor, abdominal and muscle cramps, vomiting and sweating), have occurred following abrupt discontinuance of chlordiazepoxide. The more severe withdrawal symptoms have usually been limited to those patients who had received excessive doses over an extended period of time. Generally milder withdrawal symptoms (e.g., dysphoria and insomnia) have been reported following abrupt discontinuance of benzodiazepines taken continuously at therapeutic levels for several months. Consequently, after extended therapy, abrupt discontinuation should generally be avoided and a gradual dosage tapering schedule followed. Addiction-prone individuals (such as drug addicts or alcoholics) should be under careful surveillance when receiving chlordiazepoxide or other psychotropic agents because of the predisposition of such patients to habituation and dependence.

OVERDOSAGE:

Manifestations of Chlordiazepoxide hydrochloride overdosage include somnolence, confusion, coma and diminished reflexes. Respiration, pulse and blood pressure should be monitored, as in all cases of drug overdosage, although, in general, these effects have been minimal following Chlordiazepoxide hydrochloride overdosage. General supportive measures should be employed, along with immediate gastric lavage. Intravenous fluids should be administered and an adequate airway maintained. Hypotension may be combated by the use of Levophed® (norepinephrine) or Aramine (metaraminol). Dialysis is of limited value. There have been occasional reports of excitation in patients following chlordiazepoxide hydrochloride overdosage; if this occurs barbiturates should not be used. As with the management of intentional overdosage with any drug, it should be borne in mind that multiple agents may have been ingested.

Flumazenil, a specific benzodiazepine-receptor antagonist, is indicated for the complete or partial reversal of the sedative effects of benzodiazepines and may be used in situations when an overdose with a benzodiazepine is known or suspected. Prior to the administration of flumazenil, necessary measures should be instituted to secure airway, ventilation and intravenous access. Flumazenil is intended as an adjunct to, not as a substitute for, proper management of benzodiazepine overdose. Patients treated with flumazenil should be monitored for resedation, respiratory depression and other residual benzodiazepine effects for an appropriate period after treatment. The prescriber should be aware of a risk of seizure in association with flumazenil treatment, particularly in long-term benzodiazepine users and in cyclic antidepressant overdose. The complete flumazenil package insert, including CONTRAINDICATIONS, WARNINGS and PRECAUTIONS, should be consulted prior to use.

DOSAGE AND ADMINISTRATION:

Because of the wide range of clinical indications for Chlordiazepoxide Hydrochloride Capsule the optimum dosage varies with the diagnosis and response of the individual patient. The dosage, therefore, should be individualized for maximum beneficial effects.

ADULTS | USUAL DAILY DOSE
Relief of Mild and Moderate Anxiety Disorders and Symptoms of Anxiety | 5 mg or 10 mg, 3 or 4 times daily
Relief of Severe Anxiety Disorders and Symptoms of Anxiety | 20 mg or 25 mg, 3 or 4 times daily
Geriatric Patients, or in the presence of debilitating disease. | 5 mg, 2 to 4 times daily

Preoperative Apprehension and Anxiety: On days preceding surgery, 5 to 10 mg orally, 3 or 4 times daily. If used as preoperative medication, 50 to 100 mg IM * 1 hour prior to surgery.

PEDIATRIC PATIENTS | USUAL DAILY DOSE
Because of the varied response of pediatric patients to CNS-acting drugs, therapy should be initiated with the lowest dose and increased as required. Since clinical experience in pediatric patients under 6 years of age is limited, the use of the drug in this age group is not recommended. | 5 mg, 2 to 4 times daily (may be increased in some pediatric patients to 10 mg, 2 to 3 times daily)

For the relief of withdrawal symptoms of acute alcoholism, the parenteral form * is usually used initially. If the drug is administered orally, the suggested initial dose is 50 to 100 mg, to be followed by repeated doses as needed until agitation is controlled - up to 300 mg per day. Dosage should then be reduced to maintenance levels.

*See package insert for Injectable. Chlordiazepoxide Hydrochloride.

HOW SUPPLIED:

Chlordiazepoxide Hydrochloride Capsules, USP are available in the following presentations:

5 mg hard gelatin capsules in bottles of 100 (NDC- 43547-251-10), with S251 imprinted on the opaque green cap and Solco’s logo "S" imprinted on the opaque yellow body.

10 mg hard gelatin capsules in bottles of 100 (NDC- 43547-252-10), with S252 imprinted on the opaque black cap and Solco’s logo "S" imprinted on the opaque green body.

25 mg hard gelatin capsules in bottles of 100 (NDC- 43547-253-10), with S253 imprinted on the opaque green cap and Solco’s logo "S" imprinted on the opaque white body.

Store at 25°C (77°F); excursions permitted to 15°C – 30°C (59°F – 86°F). [see USP Controlled Room Temperature].

Manufactured by:
Epic Pharma, LLC
Laurelton, NY 11413

Distributed by:
Solco Healthcare U.S., LLC
Cranbury, NJ 08512

Rev. 10/12
OE1413

MEDICATION GUIDE

This Medication Guide has been approved by the U.S. Food and Drug Administration Issued: 8/2016

PRINCIPAL DISPLAY PANEL - 10 mg

NDC 67046-912-30

Rx only

Chlordiazepoxide Hydrochloride USP CIV
10 mg 30 Capsules

Each capsule contains 10 mg of chlordiazepoxide hydrochloride USP.

See enclosed package insert for dosage information.

Keep this and all drugs out of reach of children.

Store at 25º C (77º F); excursions permitted to 15-30º C (59-86º F)

Dispense in a tight, light-resistant container, with a child resistant closure, as defined in USP/NF.

Manufactured by:
Epic Pharma, LLC
Laurelton, NY 11413

Distributed by:
Solco Healthcare U.S., LLC

2002 Eastpark Blvd.
Cranbury, NJ 08512

Iss. 06/12 LE2533

www.solcohealthcare.com

Repackaged by:
Contract Pharmacy Services-PA
125 Titus Ave Suite 200
Warrington, PA 18976 USA

PRINCIPAL DISPLAY PANEL - 25 mg

NDC 67046-935-30 Rx only

Chlordiazepoxide Hydrochloride USP CIV
25 mg 3 0 Capsules

Each capsule contains 25 mg of chlordiazepoxide hydrochloride USP.

See enclosed package insert for dosage information.

Keep this and all drugs out of reach of children.

Store at 25º C (77º F); excursions permitted to 15-30º C (59-86º F)

Dispense in a tight, light-resistant container, with a child resistant closure, as defined in USP/NF.

Manufactured by:
Epic Pharma, LLC
Laurelton, NY 11413

Distributed by:
Solco Healthcare U.S., LLC
2002 Eastpark Blvd.
Cranbury, NJ 08512

Iss. 06/12 LE2540

www.solcohealthcare.com

Repackaged by:
Contract Pharmacy Services-PA
125 Titus Ave Suite 200
Warrington, PA 18976 USA